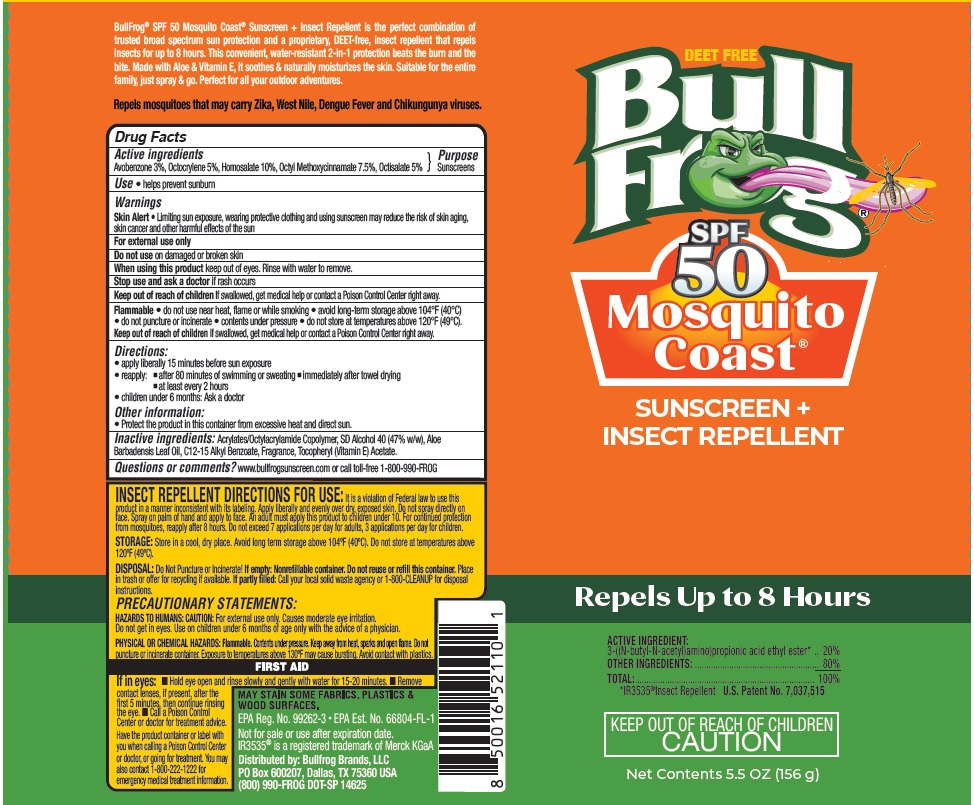 DRUG LABEL: Sunscreen and insect repellent
NDC: 77714-003 | Form: AEROSOL, SPRAY
Manufacturer: Bullfrog Brands, LLC
Category: otc | Type: HUMAN OTC DRUG LABEL
Date: 20250109

ACTIVE INGREDIENTS: AVOBENZONE 30 mg/1 g; HOMOSALATE 100 mg/1 g; OCTISALATE 50 mg/1 g; OCTOCRYLENE 50 mg/1 g; OCTINOXATE 75 mg/1 g
INACTIVE INGREDIENTS: ALOE VERA LEAF; ALKYL (C12-15) BENZOATE; .ALPHA.-TOCOPHEROL ACETATE

Bull Frog SPF50 Mosquito Coast- Sunscreen+ Inspect Repellent

Active ingredients

Avobenzone 3.0%, Octocrylene 5%, Homosalate 10.0%, Octyl methoxycinnamate 7.5%, Octisalate 5%

Purpose

Sunscreen

Uses

- helps prevent sunburn

Warnings

For external use only

Skin Alert • Limiting sun exposure, wearing protective clothing, and using sunscreen may reduce the risk of skin aging,
skin cancer and other harmful effects of the sun

FLAMMABLE:

• do not use near heat, flame or while smoking

• avoid long term storage above 104°F (40°C)

• do not puncture or incinerate

• contents under pressure

• do not store at temperatures above 120°F (49°C).

Do not use • on damaged or broken skin.

When using this product • keep out of eyes. Rinse with water to remove.

Stop use and ask a doctor if • rash occurs.

Keep out of reach of children. If swallowed, get medical help or contact a Poison Control Center right away.

Directions

- apply liberally 15 minutes before sun exposure
- reapply:

• after 80 minutes of swimming or sweating

• immediately after towel drying

• at least every 2 hours

- children under 6 months of age: ask a doctor

Other information

• Protect the product in this container from excessive heat and direct sun.

Inactive ingredients

Acrylates/Octylacrylamide Copolymer, SD Alcohol 40 (47% w/w), AloeBarbadensis Leaf Oil, C12-15 Alkyl Benzoate, Fragrance, Tocopheryl (Vitamin E) Acetate.

Questions or Comments?

www.bullfrogsunscreen.com or call toll-free 1-800-990-FROG